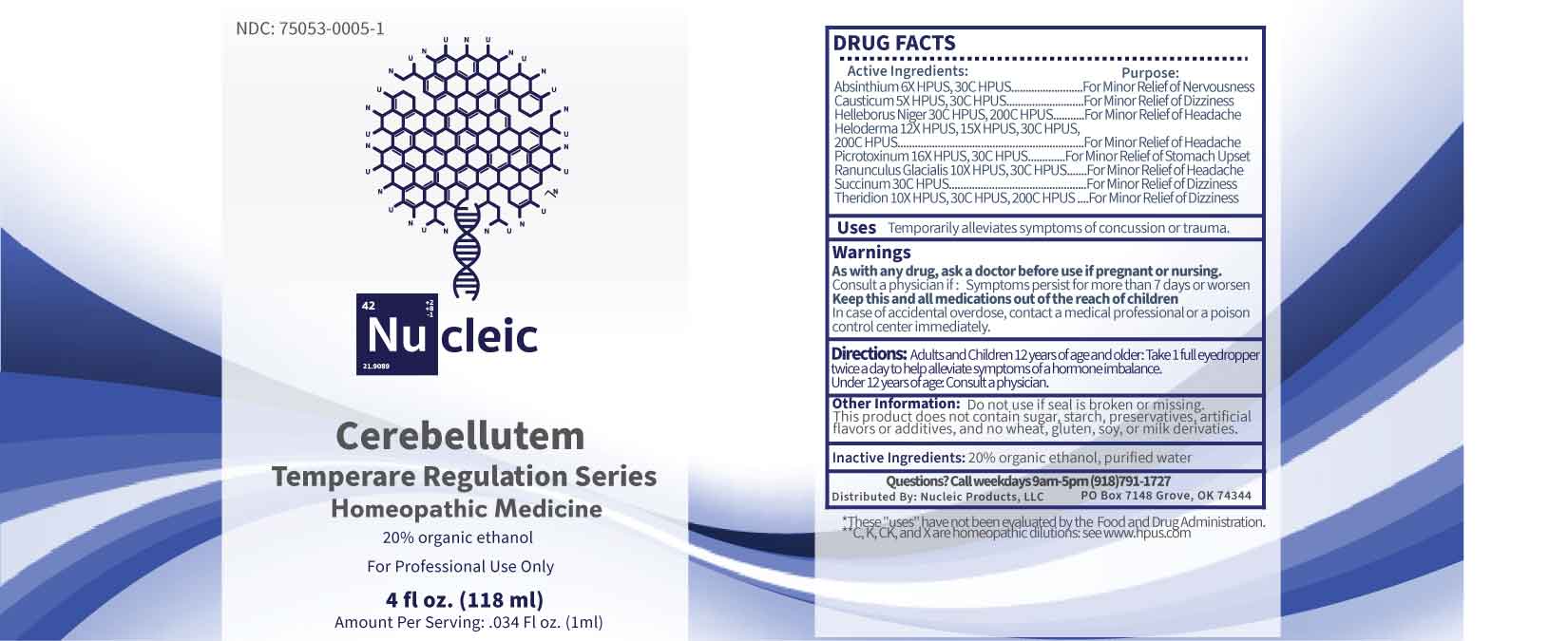 DRUG LABEL: Cerebellutem
NDC: 75053-0005 | Form: LIQUID
Manufacturer: Nucleic Products, LLC
Category: homeopathic | Type: HUMAN OTC DRUG LABEL
Date: 20250408

ACTIVE INGREDIENTS: CAUSTICUM 5 [hp_X]/1 mL; WORMWOOD 6 [hp_X]/1 mL; RANUNCULUS GLACIALIS WHOLE 10 [hp_X]/1 mL; THERIDION CURASSAVICUM 10 [hp_X]/1 mL; HELODERMA HORRIDUM VENOM 12 [hp_X]/1 mL; PICROTOXIN 16 [hp_X]/1 mL; AMBER 30 [hp_C]/1 mL; HELLEBORUS NIGER ROOT 30 [hp_C]/1 mL
INACTIVE INGREDIENTS: WATER; ALCOHOL

DRUG FACTS:

ACTIVE INGREDIENTS:

Absinthium 6X HPUS, 30C HPUS, Causticum 5X HPUS, 30C HPUS, Helleborus Niger 30C HPUS, 200C HPUS, Heloderma 12X HPUS, 15X HPUS, 30C HPUS, 200C HPUS, Picrotoxinum 16X HPUS, 30C HPUS, Ranunculus Glacialis 10X HPUS, 30C HPUS, Succinum 30C HPUS, Theridion 10X HPUS, 30C HPUS, 200C HPUS.

PURPOSE:

Absinthium – For Minor Relief of Nervousness, Causticum – For Minor Relief of Dizziness, Helleborus Niger – For Minor Relief of Headache, Heloderma – For Minor Relief of Headache, Picrotoxinum – For Minor Relief of Stomach Upset, Ranunculus Glacialis – For Minor Relief of Headache, Succinum – For Minor Relief of Dizziness, Theridion – For Minor Relief of Dizziness

USES:

Temporarily alleviates symptoms of concussion or trauma.
*These “uses” have not been evaluated by the Food and Drug Administration.

WARNINGS:

As with any drug, ask a doctor before use if pregnant or nursing.

Consult a physician if: Symptoms persist for more than 7 days or worsen

Keep this and all medications out of the reach of children.

In case of accidental overdose, contact a medical professional or a poison Control Center immediately.

Do not use if seal is broken or missing.

This Product does not contain sugar, starch, preservatives, artificial flavors or additives, and no wheat, gluten, soy, or milk derivatives.

KEEP OUT OF REACH OF CHILDREN:

In case of accidental overdose, contact a medical professional or a poison Control Center immediately.

DIRECTIONS:

Adults and Children 12 years of age and older: Take 1 full eyedropper twice a day to help alleviate symptoms of a hormone imbalance.
Under 12 years of age: Consult a physician.

INACTIVE INGREDIENTS

20% organic ethanol, purified water

QUESTIONS:

Distributed by:
Nucleic Products, LLC

PO Box 7148 Grove, OK 74344

Call weekdays 9am-5pm (918)791-1727

**C, K, CK, and X are homeopathic dilutions: See WWW.hpus.com

PACKAGE LABEL DISPLAY:

NDC: 75053-0005-1

Nu cleic

Cerebellutem

Temperare Regulation Series

Homeopathic Medicine

For Professional Use Only

4 fl oz. (118 ml)